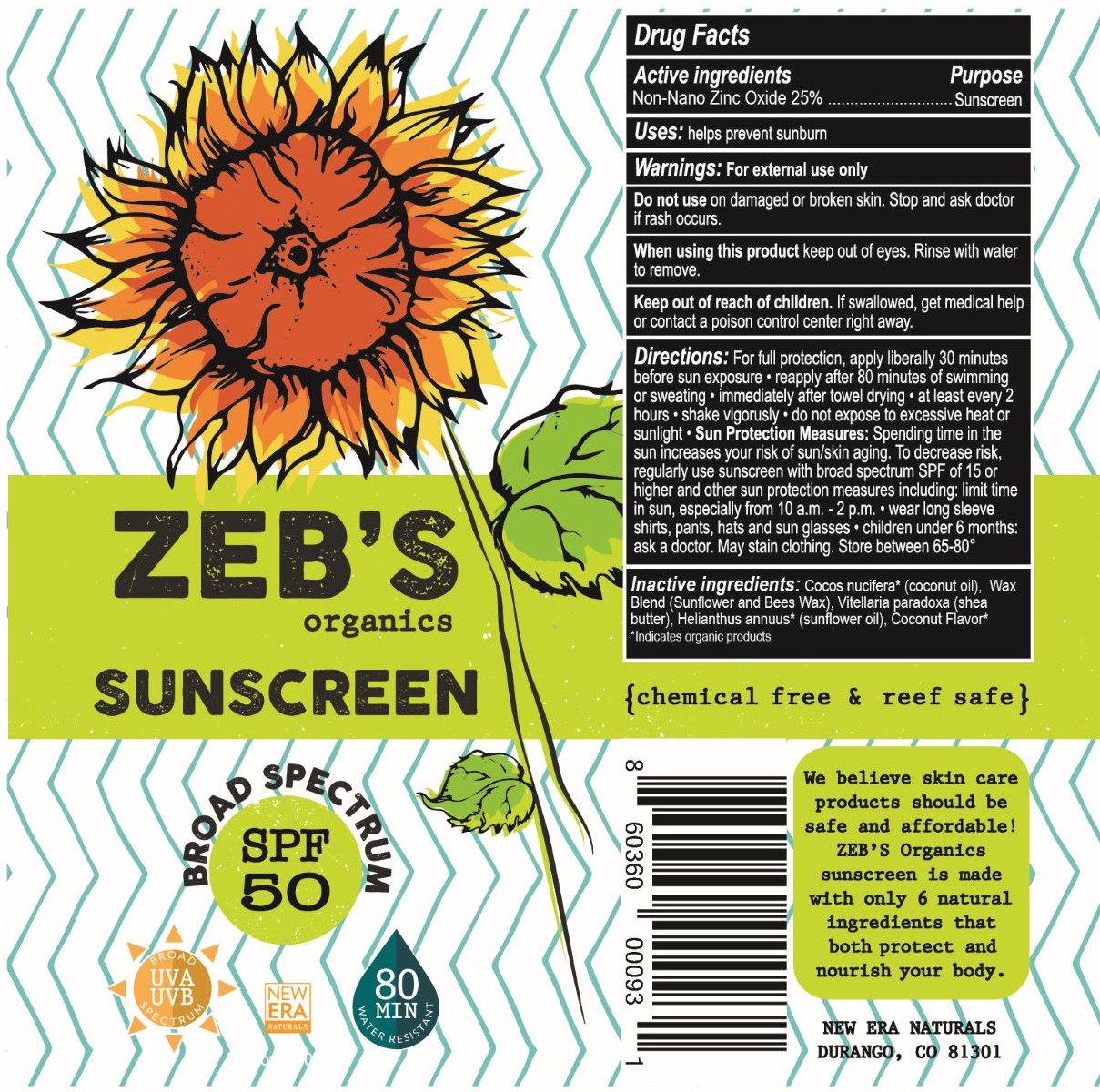 DRUG LABEL: Zebs Organics Sunscreen
NDC: 70397-2019 | Form: LOTION
Manufacturer: New Era Naturals
Category: otc | Type: HUMAN OTC DRUG LABEL
Date: 20181106

ACTIVE INGREDIENTS: ZINC OXIDE 22 g/90 g
INACTIVE INGREDIENTS: SUNFLOWER OIL 28 g/90 g; COCONUT OIL 21 g/90 g; WHITE WAX 10 g/90 g; SHEA BUTTER 9 g/90 g

Zebs SPF 50 3.4oz tube broad spectrum sunscreen